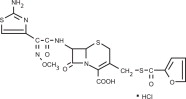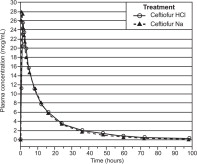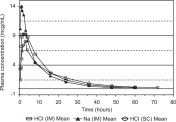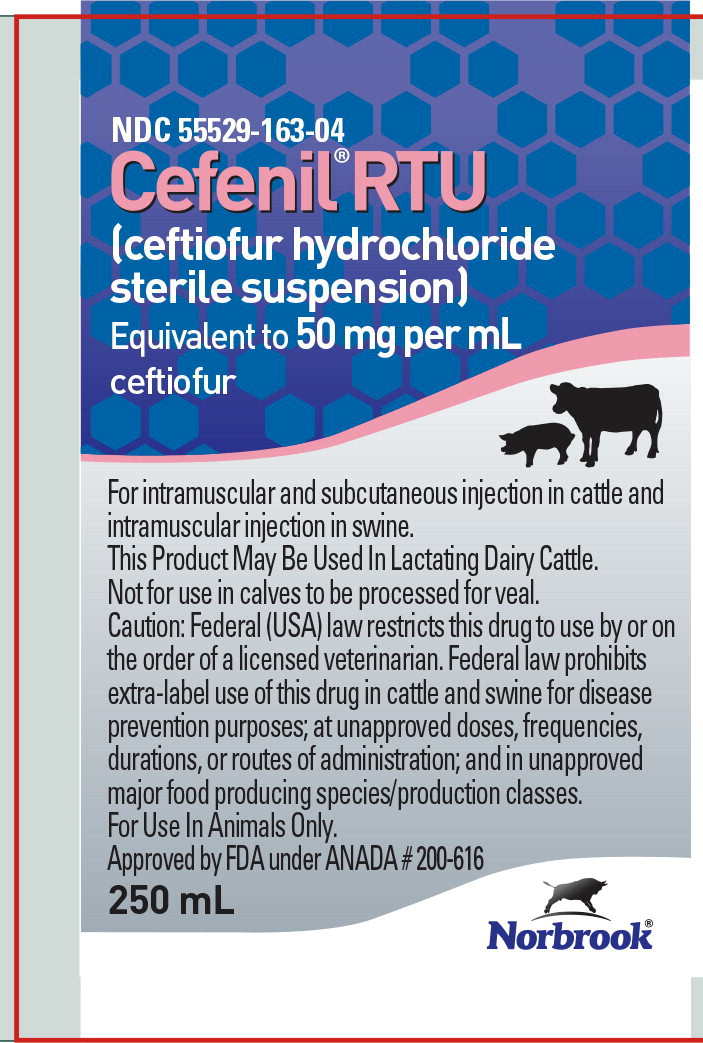 DRUG LABEL: Cefenil RTU
NDC: 55529-163 | Form: SUSPENSION
Manufacturer: Norbrook Laboratories Limited
Category: animal | Type: PRESCRIPTION ANIMAL DRUG LABEL
Date: 20220207

ACTIVE INGREDIENTS: ceftiofur hydrochloride 50 mg/1 mL

Cefenil® RTU
(ceftiofur hydrochloride sterile suspension)

For intramuscular and subcutaneous use in cattle and intramuscular use in swine. This product may be used in lactating dairy cattle. Not for use in calves to be processed for veal.

CAUTION: Federal (USA) law restricts this drug to use by or on the order of a licensed veterinarian. Federal law prohibits extra-label use of this drug in cattle and swine for disease prevention purposes; at unapproved doses, frequencies, durations, or routes of administration; and in unapproved major food producing species/production classes.

DESCRIPTION

CEFENIL® RTU (ceftiofur hydrochloride sterile suspension) is a ready to use formulation that contains the hydrochloride salt of ceftiofur, which is a broad spectrum cephalosporin antibiotic. Each mL of this ready-to-use sterile suspension contains ceftiofur hydrochloride equivalent to 50 mg ceftiofur, 5.73 mg aluminum monostearate, 1.03 mg sorbitan monooleate and medium chain triglycerides.

Structure:

Figure 1

Chemical Name of Ceftiofur Hydrochloride: 5-Thia-1-azabicyclo[4,2.0]oct-2-ene-2carboxylic acid, 7-[[(2-amino-4-thiazolyl)(methoxyimino)-acetyl]amio]-3-[[(2-furanylcarbonyl) thio]methyl]-8-oxo-, hydrochloride salt [6R-[6α,7β(Z)]]-

INDICATIONS

Swine: CEFENIL RTU is indicated for treatment/control of swine bacterial respiratory disease (swine bacterial pneumonia) associated with Actinobacillus (Haemophilus) pleuropneumoniae, Pasteurella multocida, Salmonella choleraesuis and Streptococcus suis.

Cattle: CEFENIL RTU is indicated for treatment of the following bacterial diseases:

- Bovine respiratory disease (BRD, shipping fever, pneumonia) associated with Mannheimia haemolytica, Pasteurella multocida and Histophilus somni.
- Acute bovine interdigital necrobacillosis (foot rot, pododermatitis) associated with Fusobacterium necrophorum and Bacteroides melaninogenicus.
- Acute metritis (0 to 14 days post-partum) associated with bacterial organisms susceptible to ceftiofur.

DOSAGE AND ADMINISTRATION

Shake for 90 seconds to ensure complete resuspension before using.

Swine: Administer intramuscularly at a dosage of 1.36 to 2.27 mg ceftiofur equivalents/lb (3.0 to 5.0 mg/kg) BW (1 mL of sterile suspension per 22 to 37 lb BW). Treatment should be repeated at 24 h intervals for a total of three consecutive days.

Cattle: - For bovine respiratory disease and acute bovine interdigital necrobacillosis: administer by intramuscular or subcutaneous administration at the dosage of 0.5 to 1.0 mg ceftiofur equivalents/lb (1.1 to 2.2 mg/kg) BW (1 to 2 mL sterile suspension per 100 lb BW). Administer daily at 24 h intervals for a total of three consecutive days. Additional treatments may be administered on Days 4 and 5 for animals which do not show a satisfactory response (not recovered) after the initial three treatments. In addition, for BRD only, administer intramuscularly or subcutaneously 1.0 mg ceftiofur equivalents/lb (2.2 mg/kg) BW every other day on Days 1 and 3 (48 h interval). Do not inject more than 15 mL per injection site.

Selection of dosage level (0.5 to 1.0 mg/lb) and regimen/duration (daily or every other day for BRD only) should be based on an assessment of the severity of disease, pathogen susceptibility and clinical response.

- For acute post-partum metritis: administer by intramuscular or subcutaneous administration at the dosage of 1.0 mg ceftiofur equivalents/lb (2.2 mg/kg) BW (2 mL sterile suspension per 100 lb BW). Administer at 24 h intervals for five consecutive days. Do not inject more than 15 mL per injection site.

CONTRAINDICATIONS

As with all drugs, the use of CEFENIL RTU is contraindicated in animals previously found to be hypersensitive to the drug.

WARNINGS

NOT FOR HUMAN USE. KEEP OUT OF REACH OF CHILDREN.

Penicillins and cephalosporins can cause allergic reactions in sensitized individuals. Topical exposures to such antimicrobials, including ceftiofur, may elicit mild to severe allergic reactions in some individuals. Repeated or prolonged exposure may lead to sensitization. Avoid direct contact of the product with the skin, eyes, mouth, and clothing. Persons with a known hypersensitivity to penicillin or cephalosporins should avoid exposure to this product. In case of accidental eye exposure, flush with water for 15 minutes. In case of accidental skin exposure, wash with soap and water. Remove contaminated clothing. If allergic reaction occurs (e.g., skin rash, hives, difficult breathing), seek medical attention. The safety data sheet contains more detailed occupational safety information. To report suspected adverse drug events, for technical assistance or to obtain a copy of the safety data sheet (SDS), contact Norbrook at 1-866-591-5777. For additional information about adverse drug experience reporting for animal drugs, contact FDA at 1-888-FDA-VETS or online at www.fda.gov/reportanimalae.

RESIDUE WARNINGS:

Swine: When used according to label indications, dosage, and route of administration, treated swine must not be slaughtered for 4 days following the last treatment.

Use of dosages in excess of those indicated or by unapproved routes of administration may result in illegal residues in edible tissues.

Cattle: When used according to label indications, dosage and route of administration, treated cattle must not be slaughtered for 3 days following the last treatment. When used according to label indications, dosage and route of administration, a milk discard time is not required. Uses of dosages in excess of those indicated or by unapproved routes of administration, such as intramammary, may result in illegal residues in edible tissues and/or milk. A withdrawal period has not been established in pre-ruminating calves. Do not use in calves to be processed for veal.

PRECAUTIONS

The effects of ceftiofur on cattle and swine reproductive performance, pregnancy, and lactation have not been determined.

Swine: Areas of discoloration associated with the injection site at time periods of 11 days or less may result in trim-out of edible tissues at slaughter. The safety of ceftiofur has not been demonstrated for pregnant swine or swine intended for breeding.

Cattle: Following intramuscular or subcutaneous administration in the neck, areas of discoloration at the site may persist beyond 11 days resulting in trim loss of edible tissues at slaughter. Following intramuscular administration in the rear leg, areas of discoloration at the injection site may persist beyond 28 days resulting in trim loss of edible tissues at slaughter.

CLINICAL PHARMACOLOGY

Swine: Ceftiofur administered as either ceftiofur sodium or ceftiofur hydrochloride is metabolized rapidly to desfuroylceftiofur, the primary metabolite.

Administration of ceftiofur to swine as either the sodium or hydrochloride salt provides effective concentrations of ceftiofur and desfuroylceftiofur metabolites in plasma above the MIC90 for the labeled pathogens: Actinobacillus pleuropneumoniae, Pasteurella multocida, Streptococcus suis and Salmonella choleraesuis for the 24 hour (h) period between the dosing intervals. The MIC90 for Salmonella choleraesuis (1.0 μg/mL) is higher than the other three pathogens and plasma concentrations exceed this value for the entire dosing interval only after the 2.27 mg/lb (5.0 mg/kg) body weight (BW) dose.

Comparative Bioavailability Summary

Comparable plasma concentrations of ceftiofur administered as ceftiofur hydrochloride sterile suspension or ceftiofur sodium sterile solution were demonstrated after intramuscular administration of 2.27 mg ceftiofur equivalents/lb (5.0 mg/kg) BW. See Table 1 and Figure 2.

Table 1. Swine plasma concentrations and related parameters * of ceftiofur and desfuroylceftiofur metabolites after ceftiofur hydrochloride sterile suspension, 50 mg/mL, or ceftiofur sodium sterile powder, 50 mg/mL, administered at 2.27 mg/lb ceftiofur equivalents /lb (5.0 mg/kg) BW IM.
 | Ceftiofur hydrochloride | Ceftiofur sodium
Cmax μg/mL: | 26.1 ± 5.02 | 29.2 ± 5.01
tmax h: | 0.66 – 2.0 (range) | 0.33 – 2.0 (range)
AUC0-LOQ μg·h/mL: t1/2 h: | 321 ± 50.2 16.2 ± 1.55 | 314 ± 55.1 14.0 ± 1.23
C24 h μg/mL: | 3.45 ± 0.431 | 3.53 ± 0.791
C72 h μg/mL: | 0.518 ± 0.126 | 0.407 ± 0.0675
t>0.2 h: | 93.8 ± 7.98 | 85.0 ± 7.71
Definitions:
Cmax - maximum plasma concentration in μg/mL.
tmax - the time after initial injection to when Cmax occurs, measured in hours.
AUC0-LOQ -the area under the plasma concentration vs. time curve from time of injection to the limit of quantitation of the assay (0.15 μg/mL).
t1/2 - the plasma half life of the drug in hours.
C24 h - the concentration of drug at 24 h after administration.
C72 h - the concentration of drug at 72 h after administration.
t>0.2 - the time (in hours) plasma concentrations remain above 0.2 μg/mL.
* Due to significant period effect and significant sequence effect in this study, data from period 1 only were used to evaluate these parameters.

Figure 2. Swine plasma concentrations of ceftiofur and desfuroylceftiofur metabolites after ceftiofur hydrochloride sterile suspension, 50 mg/mL, or ceftiofur sodium sterile powder, 50 mg/mL, were administered intramuscularly at 2.27 mg ceftiofur equivalents/lb (5.0 mg/kg) BW.

Concentrations of total ceftiofur in the lungs of pigs administered radiolabeled ceftiofur at 2.27 or 3.41 mg ceftiofur equivalents/lb (5.0 or 7.5 mg/kg) BW 12 h after the last of three daily intramuscular injections at 24 h intervals averaged 3.66 and 5.63 μg/g.

Cattle: Ceftiofur administered as either ceftiofur sodium or ceftiofur hydrochloride is metabolized rapidly to desfuroylceftiofur, the primary metabolite. Administration of ceftiofur to cattle as either the sodium or hydrochloride salt provides effective concentrations of ceftiofur and desfuroylceftiofur metabolites in plasma above the MIC90 for the bovine respiratory disease (BRD) label pathogens Mannheimia haemolytica, Pasteurella multocida and Histophilus somni for at least 48 h. The relationship between plasma concentrations of ceftiofur and desfuroylceftiofur metabolites above the MIC90 in plasma and efficacy has not been established for the treatment of bovine interdigital necrobacillosis (foot rot) associated with Fusobacterium necrophorum and Bacteroides melaninogenicus.

Comparative Bioavailability Summary

The comparability of plasma concentrations of ceftiofur following administration of ceftiofur hydrochloride sterile suspension or ceftiofur sodium sterile solution was demonstrated after intramuscular or subcutaneous administration of ceftiofur hydrochloride and intramuscular administration of ceftiofur sodium at 1.0 mg ceftiofur equivalents/lb (2.2 mg/kg) BW. See Table 2 and Figure 3.

Table 2. Cattle plasma concentrations and related parameters of ceftiofur and desfuroylceftiofur metabolites after ceftiofur hydrochloride sterile suspension, 50 mg/mL, administered intramuscularly or subcutaneously at 1.0 mg ceftiofur equivalents /lb (2.2 mg/kg) BW and ceftiofur sodium sterile powder, 50 mg/mL, administered intramuscularly at 1.0 mg ceftiofur equivalents /lb (2.2 mg/kg) BW.
 | Ceftiofur hydrochloride |  | Ceftiofur sodium
 | IM | SC | IM*
Cmax μg/mL | 11.0 ± 1.69 | 8.56 ± 1.89 | 14.4–16.5
tmax h | 1–4 (range) | 1-5 (range) | 0.33–3.0
t>0.2 h | 60.5 ± 6.27 | 51.0 ± 6.53 | 50.7–50.9
AUC0-LOQ μg·h/mL | 160 ± 30.7 | 95.4 ± 17.8 | 115–142
t1/2 h | 12.0 ± 2.63 | 11.5 ± 2.57 | 9.50–11.1
C24 h μg/mL | 1.47 ± 0.380 | 0.926 ± 0.257 | 0.86–1.16
C48 h μg/mL | 0.340 ± 0.110 | 0.271 ± 0.086 | 0.250–0.268
Definitions:
Cmax - maximum concentration of drug in plasma in μg/mL. tmax - the time after initial injection to when Cmax occurs, measured in hours. t>0.2 - the time (in hours) plasma drug concentrations remain above 0.2 μg/mL. AUC0-LOQ -the area under the plasma drug concentrations vs. time curve from time of injection to the limit of quantitation of the assay (0.15 μg/mL). t1/2 - the drug half life in plasma expressed in hours. C24 h - the plasma drug concentration 24 h after administration. C48 h - the plasma drug concentration 48 h after administration. * Values represent the separate means from each study.

Figure 3. Cattle plasma concentrations of ceftiofur and desfuroylceftiofur metabolites after ceftiofur hydrochloride sterile suspension, 50 mg/mL, was administered either intramuscularly or subcutaneously or ceftiofur sodium sterile powder, 50 mg/mL, was administered intramuscularly at 1.0 mg ceftiofur equivalents/lb (2.2 mg/kg) BW.

Total residues of ceftiofur were measured in the lungs of cattle administered radiolabeled ceftiofur at 1.0 mg ceftiofur equivalents/lb (2.2 mg/kg) BW at 24 h intervals for five consecutive days. Twelve h after the fifth injection of ceftiofur hydrochloride, total ceftiofur concentrations in the lung averaged 1.15 μg/g, while total ceftiofur concentrations in the lung 8 h after the fifth ceftiofur sodium injection averaged 1.18 μg/g.

CLINICAL MICROBIOLOGY

CEFENIL RTU is a ready to use formulation that contains the hydrochloride salt of ceftiofur, which is a broad spectrum cephalosporin antibiotic active against gram-positive and gram-negative bacteria including β-lactamase-producing strains. Like other cephalosporins, ceftiofur is bacteriocidal, in vitro, resulting in inhibition of cell wall synthesis.

Swine: Studies with ceftiofur have demonstrated in vitro and in vivo activity against gram-negative pathogens, including Actinobacillus (Haemophilus) pleuropneumoniae, Pasteurella multocida, Salmonella choleraesuis, and the gram-positive pathogen Streptococcus suis, all of which can be associated with swine bacterial respiratory disease – SRD (swine bacterial pneumonia). A summary of the minimum inhibitory concentration (MIC) values from SRD pathogens isolated from clinical field effectiveness studies is found in Table 3. Historic diagnostic laboratory MIC values for SRD pathogens from the US and Canada are found in Table 4.

Cattle: Studies with ceftiofur have demonstrated in vitro and in vivo activity against Mannheimia haemolytica, Pasteurella multocida and Histophilus somni, the three major pathogenic bacteria associated with bovine respiratory disease (BRD, pneumonia, shipping fever), and against Fusobacterium necrophorum and Bacteroides melaninogenicus, two of the major pathogenic anaerobic bacteria associated with acute bovine interdigital necrobacillosis (foot rot, pododermatitis).

A summary of the MIC values for BRD and foot rot pathogens isolated from clinical field effectiveness studies is found in Table 3. Historic diagnostic MIC values for BRD and foot rot pathogens from the US and Canada are found in Table 4.

Antimicrobial Susceptibility

Summaries of MIC data are presented in Tables 3 and 4. Testing followed Clinical and Laboratory Standards Institute (CLSI) Guidelines.

Table 3. Ceftiofur MIC Values of Bacterial Isolates from Clinical Field Studies in the USA
Animal | Organism | Number Tested | Date Tested | MIC 90* (μg/mL) | MIC Range (μg/mL)
Bovine | Mannheimia haemolytica | 461 | 1988-1992 | 0.06 | ≤0.03-0.13
Bovine | Mannheimia haemolytica | 42 | 1993 | 0.015 | ≤0.003-0.03
Bovine | Pasteurella multocida | 318 | 1988 -1992 | 0.06 | ≤0.03-0.25
Bovine | Pasteurella multocida | 48 | 1993 | ≤0.003 | ≤0.003-0.015
Bovine | Histophilus somni | 109 | 1988 -1992 | 0.06 | ≤0.03-0.13
Bovine | Histophilus somni | 59 | 1993 | ≤0.0019 | no range
Bovine | Fusobacterium necrophorum | 17 | 1994 | ≤0.06 | no range
Swine | Actinobacillus pleuropn. | 83 | 1993 | ≤0.03 | ≤0.03-0.06
Swine | Pasteurella multocida | 74 | 1993 | ≤0.03 | ≤0.03-0.06
Swine | Streptococcus suis | 94 | 1993 | 0.25 | ≤0.03-1.0
Swine | Salmonella choleraesuis | 50 | 1993 | 1.0 | 1.0-2.0
Swine | beta–hemolytic Streptococcus spp. | 24 | 1993 | ≤0.03 | ≤0.03-0.06
Swine | Actinobacillus suis | 77 | 1998 | 0.0078 | 0.0019-0.0078
Swine | Haemophilus parasuis | 76 | 1998 | 0.06 | 0.0039-0.25
*Minimum inhibitory concentration (MIC) for 90% of the isolates

Table 4. Ceftiofur MIC Values of Bacterial Isolates from Diagnostic Laboratories* in the USA and Canada
Animal | Organism | Number Tested | Date Tested | MIC 90** (μg/mL) | MIC Range (μg/mL)
Bovine | Mannheimia haemolytica | 110 | 1997-1998 | 0.06 | ≤0.03-0.25
Bovine | Mannheimia haemolytica | 139 | 1998-1999 | ≤0.03 | ≤0.03-0.5
Bovine | Mannheimia haemolytica | 209 | 1999-2000 | ≤0.03 | ≤0.03-0.12
Bovine | Mannheimia haemolytica | 189 | 2000-2001 | ≤0.03 | ≤0.03-0.12
Bovine | Pasteurella multocida | 107 | 1997-1998 | ≤0.03 | ≤0.03-0.25
Bovine | Pasteurella multocida | 181 | 1998-1999 | ≤0.03 | ≤0.03-0.5
Bovine | Pasteurella multocida | 208 | 1999-2000 | ≤0.03 | ≤0.03-0.12
Bovine | Pasteurella multocida | 259 | 2000-2001 | ≤0.03 | ≤0.03-0.12
Bovine | Histophilus somni | 48 | 1997-1998 | ≤0.03 | ≤0.03-0.25
Bovine | Histophilus somni | 87 | 1998-1999 | ≤0.03 | ≤0.03-0.125
Bovine | Histophilus somni | 77 | 1999-2000 | ≤0.03 | ≤0.03-0.06
Bovine | Histophilus somni | 129 | 2000-2001 | ≤0.03 | ≤0.03-0.12
Bovine | Bacteroides fragilis group | 29 | 1994 | 16.0 | ≤0.06->16.0
Bovine | Bacteroides spp., non-fragilis group | 12 | 1994 | 16.0 | 0.13->16.0
Bovine | Peptostreptococcus anaerobius | 12 | 1994 | 2.0 | 0.13-2.0

Table 4. Continuation
Animal | Organism | Number Tested | Date Tested | MIC 90** (μg/mL) | MIC Range (μg/mL)
Swine | Actinobacillus pleuropn. | 97 | 1997-1998 | ≤0.03 | no range
Swine | Actinobacillus pleuropn. | 111 | 1998-1999 | ≤0.03 | ≤0.03-0.25
Swine | Actinobacillus pleuropn. | 126 | 1999-2000 | ≤0.03 | ≤0.03-0.06
Swine | Actinobacillus pleuropn. | 89 | 2000-2001 | ≤0.03 | ≤0.03-0.06
Swine | Pasteurella multocida | 114 | 1997-1998 | ≤0.03 | ≤0.03-1.0
Swine | Pasteurella multocida | 147 | 1998-1999 | ≤0.03 | ≤0.03-0.5
Swine | Pasteurella multocida | 173 | 1999-2000 | ≤0.03 | ≤0.03-0.06
Swine | Pasteurella multocida | 186 | 2000-2001 | ≤0.03 | ≤0.03-0.12
Swine | Streptococcus suis | 106 | 1997-1998 | 0.5 | ≤0.03-4.0
Swine | Streptococcus suis | 142 | 1998-1999 | 0.25 | ≤0.03-1.0
Swine | Streptococcus suis | 146 | 1999-2000 | 0.06 | ≤0.03-4.0
Swine | Streptococcus suis | 167 | 2000-2001 | 0.06 | ≤0.03-4.0
Swine | Salmonella choleraesuis | 96 | 1999-2000 | 1.0 | 0.03->4.0
Swine | Salmonella choleraesuis | 101 | 2000-2001 | 1.0 | 0.5-2.0
*The following in vitro data are available but their clinical significance is unknown. **Minimum inhibitory concentration (MIC) for 90% of the isolates

Based on the pharmacokinetic studies of ceftiofur in swine and cattle after a single intramuscular injection of 1.36 to 2.27 mg ceftiofur equivalents/lb (3.0 to 5.0 mg/kg) BW (swine) or 0.5 to 1.0 mg ceftiofur equivalents/lb (1.1 to 2.2 mg/kg) BW (cattle) and the MIC and disk (30 μg) diffusion data, the following breakpoints are recommended by CLSI.

Zone Diameter (mm) | MIC (μg/mL) | Interpretation
≥ 21 | ≤ 2.0 | (S) Susceptible
18-20 | 4.0 | (I) Intermediate
≤ 17 | ≥ 8.0 | (R) Resistant

A report of "Susceptible" indicates that the pathogen is likely to be inhibited by generally achievable blood levels. A report of "Intermediate" is a technical buffer zone and isolates falling into this category should be retested. Alternatively the organism may be successfully treated if the infection is in a body site where drug is physiologically concentrated. A report of "Resistant" indicates that the achievable drug concentrations are unlikely to be inhibitory and other therapy should be selected. Standardized procedures^1 require the use of laboratory control organisms for both standardized diffusion techniques and standardized dilution techniques. The 30 μg ceftiofur sodium disk should give the following zone diameters and the ceftiofur sodium standard reference powder (or disk) should provide the following MIC values for the reference strain. Ceftiofur sodium disks or powder reference standard is appropriate for both ceftiofur salts.

Table 5. Acceptable quality control ranges for ceftiofur against Clinical and Laboratory Standards Institute recommended American type Culture Collection (ATCC) reference strains
Organism name (ATCC No.) | Zone diameter* (mm) | MIC range (μg/mL)
Escherichia coli (25922) | 26-31 | 0.25-1.0
Staphylococcus aureus (29213) | - | 0.25-1.0
Staphylococcus aureus (25923) | 27-31 | -
Pseudomonas aeruginosa (27853) | 14-18 | 16.0-64.0
Actinobacillus pleuropneumoniae (27090) | 34-42** | 0.004-0.015***
Histophilus somni (700025) | 36-46** | 0.0005-0.004***
*All testing performed using a 30 μg disk.
**Quality control ranges are applicable only to tests performed by disk diffusion test using a chocolate Mueller-Hinton agar, incubated in 5-7% CO^2 for 20-24 hours.
***MIC quality control ranges are applicable only to tests performed by broth microdilution procedures using veterinary fastidious medium (VFM).

CLINICAL EFFICACY

Cattle: In addition to demonstrating comparable plasma concentrations, the following clinical efficacy data are provided.

A clinical study was conducted to evaluate the efficacy of ceftiofur hydrochloride administered subcutaneously for the treatment of the bacterial component of BRD under natural field conditions. When uniform clinical signs of BRD were present, 60 cattle (111 to 207 kg) were randomly assigned to one of the following treatment groups: negative control or ceftiofur hydrochloride at 0.5 or 1.0 ceftiofur equivalents/lb (1.1 or 2.2 mg/kg) BW. Treatments were administered daily for three consecutive days.

Cattle were evaluated daily and animals that died or were euthanatized were necropsied and the lung lesions scored. On Day 15, all surviving animals were euthanatized and necropsied and the lung lesions scored. Mortality rates were 65%, 10% and 5% for negative controls, 0.5 mg ceftiofur equivalents/lb and 1.0 mg ceftiofur equivalents/lb, (1.1 or 2.2 mg/kg) BW, respectively. Mortality rates for both ceftiofur hydrochloride treatment groups were lower than for negative controls (P < 0.0001). Rectal temperatures 24 h after third treatment were 104.0°F, 103.1°F and 102.8°F for negative controls, 0.5 mg/lb and 1.0 mg/lb (1.1 or 2.2 mg/kg) BW, respectively. The temperatures for both ceftiofur hydrochloride treatment groups were lower than the negative controls (P ≤ 0.05). Ceftiofur hydrochloride administered subcutaneously for three consecutive days at 0.5 or 1.0 mg ceftiofur equivalents/lb (1.1 or 2.2 mg/kg) BW is an effective treatment for the bacterial component of BRD. A three-location clinical field study was conducted to evaluate the efficacy of ceftiofur hydrochloride administered intramuscularly daily for three days or every other day (Days 1 and 3) for the treatment of the bacterial component of naturally occurring BRD. When uniform signs of BRD were present, 360 beef crossbred cattle were randomly assigned to one of the following treatment groups: negative control, ceftiofur sodium at 0.5 mg ceftiofur equivalents/lb (1.1 mg/kg) BW daily for three days, ceftiofur hydrochloride at 1.0 mg ceftiofur equivalents/lb (2.2 mg/kg) BW daily for three days, or ceftiofur hydrochloride at 1.0 mg ceftiofur equivalents/lb BW on Days 1 and 3 (every other day). All treatments were administered intramuscularly. All ceftiofur treatment groups (hydrochloride and sodium) and treatment regimens (every day and every other day) significantly (P<0.05) reduced Day 4 rectal temperature as compared to the negative control. Clinical success on Days 10 and 28 and mortality to Day 28 were not different for the ceftiofur groups (hydrochloride and sodium) and treatment regimens (every day and every other day). The results of this study demonstrate that daily and every other day (Days 1 and 3) intramuscular administration of ceftiofur hydrochloride are effective treatment regimens for the bacterial component of BRD. An eight location study was conducted under natural field conditions to evaluate the efficacy of ceftiofur hydrochloride for the treatment of acute post-partum metritis (0 to 14 days post-partum). When clinical signs of acute post-partum metritis (rectal temperature ≥103°F and fetid vaginal discharge) were observed, 361 lactating dairy cows were assigned randomly to treatment or negative control.

Cattle were dosed either subcutaneously or intramuscularly, daily for five consecutive days. On days 1, 5 and 9 after the last day of dose administration, cows were evaluated for clinical signs of acute post-partum metritis. A cure was defined as rectal temperature <103°F and lack of fetid discharge. Cure rate for the 1.0 mg ceftiofur equivalents/lb (2.2 mg/kg) BW dose group was significantly improved relative to cure rate of the negative control on day 9. The results of this study demonstrate that ceftiofur hydrochloride administered daily for five consecutive days at a dose of 1.0 mg ceftiofur equivalents/lb (2.2 mg/kg) BW is an effective treatment for acute post-partum metritis.

ANIMAL SAFETY

Swine: Results from a five-day tolerance study in normal feeder pigs indicated that ceftiofur sodium was well tolerated when administered at 57 mg ceftiofur equivalents/lb (125 mg/kg) (more than 25 times the highest recommended daily dosage of 2.27 mg/lb (5.0 mg/kg)) BW for five consecutive days. Ceftiofur administered intramuscularly to pigs produced no overt adverse signs of toxicity.

To determine the safety margin in swine, a safety/toxicity study was conducted. Five barrows and five gilts per group were administered ceftiofur sodium intramuscularly at 0, 2.27, 6.81 and 11.36 mg ceftiofur equivalents/lb (0, 5, 15, 25 mg/kg) BW for 15 days. This is 0, 1, 3 and 5 times the highest recommended dose of 2.27 mg/lb (5.0 mg/kg) BW/day and 5 times the recommended treatment length of 3 days. There were no adverse systemic effects observed, indicating that ceftiofur has a wide margin of safety when injected intramuscularly into feeder pigs at the highest recommended dose of 2.27 mg ceftiofur equivalents/lb (5.0 mg/kg) BW daily for 3 days or at levels up to 5 times the highest recommended dose for 5 times the recommended length of treatment.

A separate study evaluated the injection site tissue tolerance of ceftiofur hydrochloride in swine when administered intramuscularly in the neck at 1.36 and 2.27 mg ceftiofur equivalents/lb (3.0 to 5.0 mg/kg) BW. Animals were necropsied at intervals to permit evaluations at 12 h, and 3, 5, 7, 9, 11, 15, 20, and 25 days after last injection. Injection sites were evaluated grossly at necropsy. No apparent changes (swelling or inflammation) were observed clinically after 12 h post-injection. Areas of discoloration associated with the injection site were observed at time periods less than 11 days after last injection.

Cattle: Results from a five-day tolerance study in feeder calves indicated that ceftiofur sodium was well tolerated at 25 times (25 mg ceftiofur equivalents/lb {55 mg/kg} BW) the highest recommended dose of 1.0 mg ceftiofur equivalents/lb (2.2 mg/kg) BW for five consecutive days. Ceftiofur administered intramuscularly had no adverse systemic effects. In a 15-day safety/toxicity study, five steer and five heifer calves per group were administered ceftiofur sodium intramuscularly at 0 (vehicle control), 1, 3, 5 and 10 times the highest recommended dose of 1.0 mg ceftiofur equivalents/lb (2.2 mg/kg) BW to determine the safety factor.

There were no adverse systemic effects indicating that ceftiofur sodium has a wide margin of safety when injected intramuscularly into the feeder calves at 10 times (10 mg ceftiofur equivalents/lb {22 mg/kg} BW) the recommended dose for three times (15 days) the recommended length of treatment of three to five days. Local tissue tolerance to intramuscular injection of ceftiofur hydrochloride was evaluated in the following study. Results from a tissue tolerance study indicated that ceftiofur hydrochloride was well tolerated and produced no systemic toxicity in cattle when administered intramuscularly in the neck and rear leg at a dose of 1.0 mg ceftiofur equivalents/lb (2.2 mg/kg) BW at each injection site. This represents a total dose per animal of 2.0 mg ceftiofur equivalents/lb (4.4 mg/kg) BW. Clinically noted changes (local swelling) at injection sites in the neck were very infrequent (2/48 sites) whereas noted changes in rear leg sites were more frequent (21/48 sites). These changes in the rear leg injection sites were generally evident on the day following injection and lasted from 1 to 11 days. At necropsy, injection sites were recognized by discoloration of the subcutaneous tissues and muscle that resolved in approximately 7 to 15 days in the neck and 19 to 28 days in the rear leg.

Results from another tissue tolerance study indicated that ceftiofur hydrochloride was well tolerated and produced no systemic toxicity to cattle when administered subcutaneously at 0.5 or 1.0 mg ceftiofur equivalents/lb (1.1 or 2.2 mg/kg) BW at 24 h intervals for 5 days. Mild and usually transient, clinically visible or palpable reactions (local swelling) were localized at the injection site. At necropsy, injection sites were routinely recognized by edema, limited increase in thickness and color changes of the subcutaneous tissue and/or fascial surface of underlying muscle. The fascial surface of the muscle was visibly affected in most cases through 9.5 days after injection. Underlying muscle mass was not involved. There were no apparent differences in tissue response to administration of ceftiofur hydrochloride at 0.5 or 1.0 mg ceftiofur equivalents/lb (1.1 or 2.2 mg/kg) BW.

TISSUE RESIDUE DEPLETION

Swine: A pivotal tissue residue decline study was conducted in swine. In this study, pigs received 2.27 mg of ceftiofur per lb body weight (5 mg of ceftiofur per kg body weight) per day for three consecutive days. Ceftiofur residues in tissues were less than the tolerances for ceftiofur residues in tissues such as kidney, liver and muscle by 4 days after dosing. These data collectively support a 4-day pre-slaughter withdrawal period in swine when used according to label directions.

Cattle: Two pivotal tissue residue decline studies were conducted in cattle. In the first study, cattle received an intramuscular injection of 1.0 mg of ceftiofur per lb body weight (2.2 mg of ceftiofur per kg body weight) for five consecutive days. Ceftiofur residues in tissues were less than the tolerances for ceftiofur residues in tissues such as kidney, liver and muscle by 3 days after dosing. In the second study, cattle received a subcutaneous injection of 1.0 mg of ceftiofur per lb body weight (2.2 mg of ceftiofur per kg body weight) for five consecutive days. Ceftiofur residues in tissues were less than the tolerances for ceftiofur residues in tissues such as kidney, liver and muscle by 3 days after dosing. These data collectively support a 3-day pre-slaughter withdrawal period in cattle when used according to label directions. In addition, two blood-level bioequivalence studies were conducted in cattle (one using subcutaneous administration and one using intramuscular administration). Blood concentrations of ceftiofur (measured as ceftiofur free acid equivalents) were greater than the analytical method's limit of quantification through 12 hours after administration, and these data demonstrated bioequivalence between Cefenil® RTU and the referenced listed new animal drug. These data support a zero-day milk discard time in lactating dairy cows.

STORAGE CONDITIONS

Do not store above 30ºC (86ºF). Shake well before using. Protect from freezing. Contents should be used within 42 days after the first dose is removed.

HOW SUPPLIED

CEFENIL RTU is available in 100 mL and 250 mL vials.

^1 Clinical and Laboratory Standards Institute (CLSI). Performance Standards for Antimicrobial Disk and Dilution Susceptibility Tests for Bacteria Isolated from Animals; Approved Standard – Second Edition. NCCLS document M31-A2. CLSI, 940 West Valley Road, Suite 1400, Wayne, Pennsylvania 19087-1898, 2002.

Approved by FDA under ANADA # 200-616

Made in the UK
Manufactured by: Norbrook Laboratories Limited, Newry, Co. Down, BT35 6PU, Northern Ireland

® Cefenil is a registered trademark of Norbrook Laboratories Limited

Norbrook®

Principal Display Panel – 250 mL Vial Label

NDC 55529-163-04

Cefenil®RTU

(ceftiofur hydrochloride
sterile suspension)

Equivalent to 50 mg per mL
ceftiofur

For intramuscular and subcutaneous injection in cattle and intramuscular injection in swine. This Product May Be Used In Lactating Dairy Cattle. Not for use in calves to be processed for veal. Caution: Federal (USA) law restricts this drug to use by or on the order of a licensed veterinarian. Federal law prohibits extra-label use of this drug in cattle and swine for disease prevention purposes; at unapproved doses, frequencies, durations, or routes of administration; and in unapproved major food producing species/production classes.

For Use In Animals Only.

Approved by FDA under ANADA # 200-616

250 mL

Norbrook®